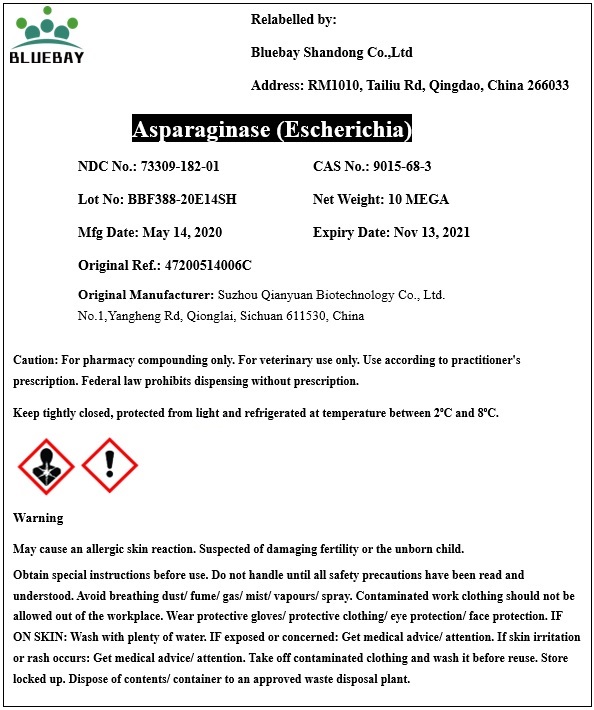 DRUG LABEL: Asparaginase (Escherichia)
NDC: 73309-182 | Form: POWDER
Manufacturer: BLUEBAY SHANDONG CO.,LTD
Category: other | Type: BULK INGREDIENT
Date: 20200901

ACTIVE INGREDIENTS: ASPARAGINASE 1 U/1 U

Asparaginase (Escherichia)